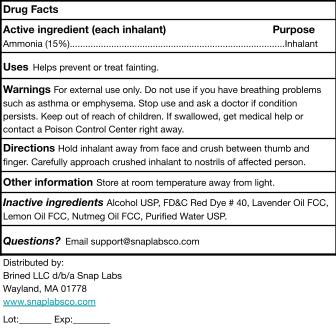 DRUG LABEL: Snap Labs 20-Count Ammonia Inhalants
NDC: 87270-002 | Form: INHALANT
Manufacturer: Brined LLC d/b/a Snap Labs
Category: otc | Type: HUMAN OTC DRUG LABEL
Date: 20251208

ACTIVE INGREDIENTS: AMMONIA 150 mg/1 mL
INACTIVE INGREDIENTS: LAVENDER OIL; LEMON OIL; NUTMEG OIL; FD&C RED NO. 40; ALCOHOL; WATER

Active Ingredients

Ammonia (15%)...Inhalant

Purpose

Inhalant

Warnings

For external use only. Do not use if you have breathing problems such as asthma or emphysema. Stop use and ask a doctor if condition persists. Keep out of reach of children. If swallowed, get medical help or contact a Poison Control Center right away.

Dosage and Administration

Hold inhalant away from face and crush between thumb and finger. Carefully approach crushed inhalant to nostrils of affected person.

Keep out of reach of children.

Do not use if you have breathing problems such as asthma or emphysema.

Inactive ingredients

Inactive ingredients Alcohol USP, FD&C Red Dye # 40, Lavender Oil FCC, Lemon Oil FCC, Nutmeg Oil FCC, Purified Water USP.

Uses

Helps prevent or treat fainting.